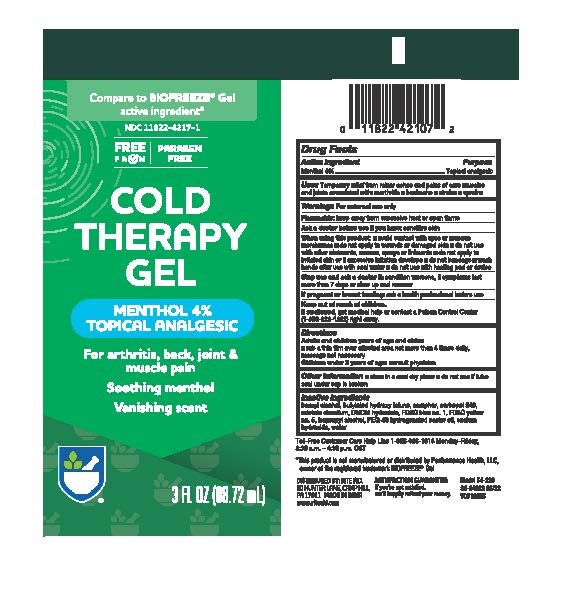 DRUG LABEL: Rite Aid Cool Therapy Gel
NDC: 11822-4217 | Form: GEL
Manufacturer: Rite Aid
Category: otc | Type: HUMAN OTC DRUG LABEL
Date: 20241219

ACTIVE INGREDIENTS: MENTHOL 40 mg/1 mL
INACTIVE INGREDIENTS: BUTYLATED HYDROXYTOLUENE; CAMPHOR (NATURAL); CARBOMER 940; EDETATE DISODIUM; DMDM HYDANTOIN; FD&C BLUE NO. 1; ISOPROPYL ALCOHOL; FD&C YELLOW NO. 5; POLYOXYL 40 HYDROGENATED CASTOR OIL; SODIUM HYDROXIDE; WATER; BENZYL ALCOHOL

Rite Aid Cool Therapy Gel

Active Ingredients

Menthol 4%

Purpose

Topical Analgesic

Uses

Temporary relief from minor aches and pains of sore muscles and joints associated with arthritis, backache, strains, sprains

Warnings

For external use only

Flammable:

Keep away from excessive heat or open flame.

Ask a doctor before use if you have:

Sensitive skin

When using this product:

Avoid contact with the eyes or mucous membranes; Do not apply to wounds or damaged skin; Do not use with other ointments, creams, sprays or liniments; Do not apply to irritated skin or if excessive irritated develops; Do not bandage; Wash hands after use with cool water; Do not use with a heating pad or device

Stop use and ask a doctor if:

Condition worsens, or if symptoms persist for more than 7 days, or clear up and reoccur

If pregnant or breast-feeding:

Ask a health professional before use

Keep out of reach of children:

If swallowed, get medical help or contact a Poison Control Center (1-800-222-1222) right away.

Directions

Adults and children 2 years of age and older: Rub a thin film over affected areas not more than 4 times daily; massage not necessary
Children under 2 years of age: Consult physician

Inactive Ingredients

benzyl alcohol, butylated hydroxy tolune, camphor, carbopol 940, edetate disodium, DMDM hydantoin, FD&C blue No.1, FD&C Yellow No. 5, Isopropyl Alcohol, PEG-40 hydrogenated castor oil, sodium hydroxide, Water

Questions or Comments

1-866-326-1313 Monday- Friday 8:30am-4:30 pm CST